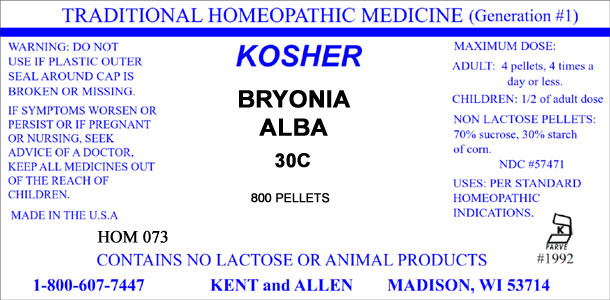 DRUG LABEL: Bryonia Alba
NDC: 57471-3061 | Form: PELLET
Manufacturer: Celletech Ltd.
Category: homeopathic | Type: HUMAN OTC DRUG LABEL
Date: 20120821

ACTIVE INGREDIENTS: BRYONIA ALBA ROOT 30 [hp_C]/1 1
INACTIVE INGREDIENTS: SUCROSE; STARCH, CORN

Bryonia Alba

WARNING

WARNING: DO NOT USE IF PLASTIC OUTER SEAL AROUND CAP BROKEN OR MISSING.

IF SYMPTOMS WORSEN OR PERSIST OR IF PREGNANT OR NURSING, SEEK ADVICE OF A DOCTOR

Keep out of reach of children

KEEP ALL MEDICINES OUT OF THE REACH OF CHILDREN.

MAXIMUM DOSE

ADULT: 4 pellets, 4 times a day or less.

CHILDREN: 1/2 of adult dose

Active Ingredient

Bryonia Alba 30C

Inactive ingredient

NON LACTOSE PELLETS:

70% sucrose, 30% starch of corn.

Usage

USES: PER STANDARD HOMEOPATHIC INDICATIONS.

Purpose

USES: PER STANDARD HOMEOPATHIC INDICATIONS.

Manufacturer Info, etc.

CONTAINS NO LACTOSE OR ANIMAL PRODUCTS

MADE IN THE U.S.A.

NDC #57471

1-800-607-7447 KENT and ALLEN MADISON, WI 53714

KOSHER

KOSHER PARVE #1992

TRADITIONAL HOMEOPATHIC MEDICINE (Generation #1)

Principal display panel

BRYONIA ALBA

30C

800 PELLETS

HOM 073